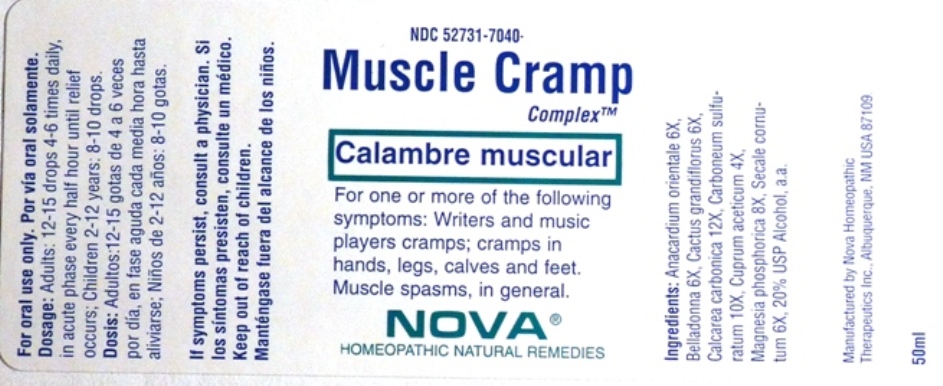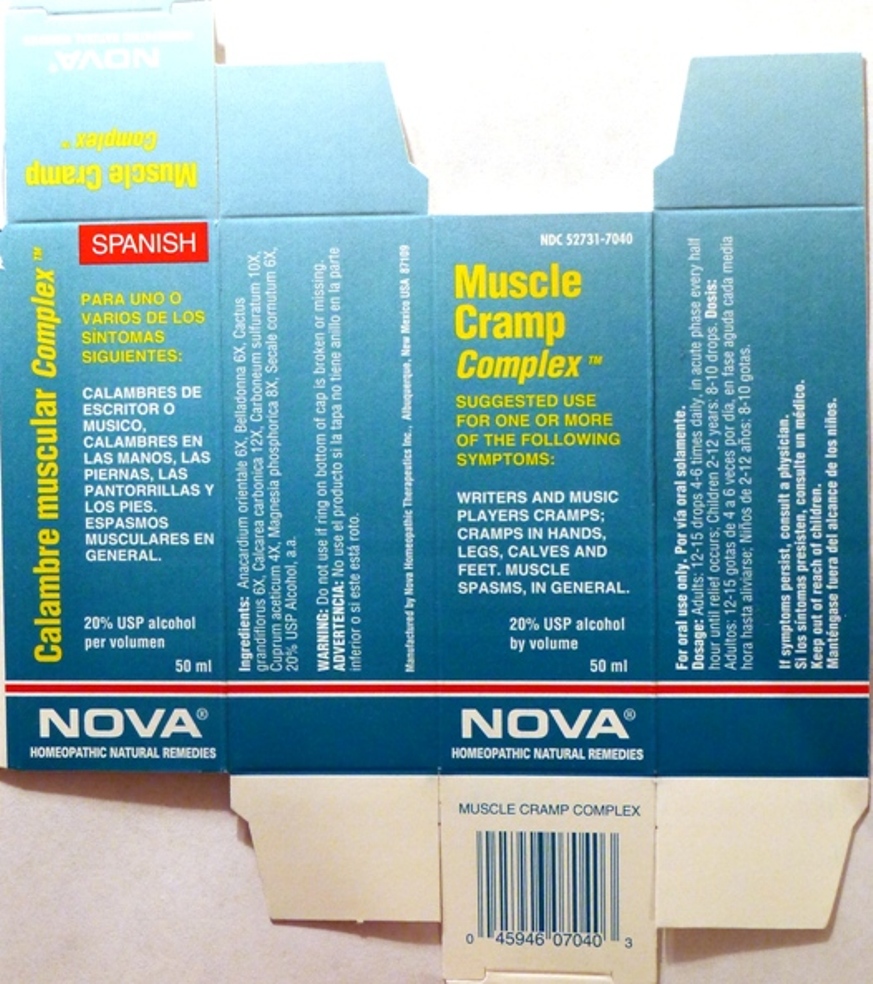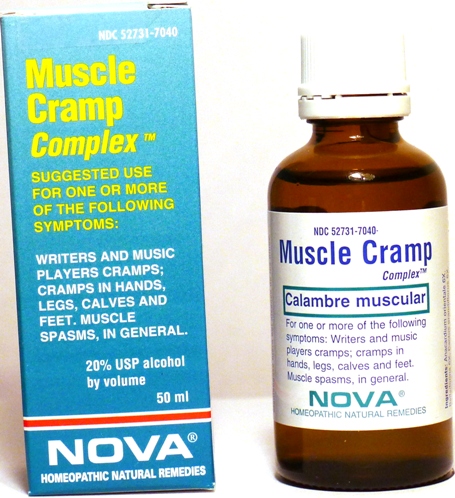 DRUG LABEL: Muscle Cramp Complex
NDC: 52731-7040 | Form: LIQUID
Manufacturer: Nova Homeopathic Therapeutics, Inc.
Category: homeopathic | Type: HUMAN OTC DRUG LABEL
Date: 20110601

ACTIVE INGREDIENTS: SEMECARPUS ANACARDIUM JUICE 6 [hp_X]/1 mL; ATROPA BELLADONNA 6 [hp_X]/1 mL; SELENICEREUS GRANDIFLORUS STEM 6 [hp_X]/1 mL; OYSTER SHELL CALCIUM CARBONATE, CRUDE 12 [hp_X]/1 mL; CARBON DISULFIDE 10 [hp_X]/1 mL; CUPRIC ACETATE 4 [hp_X]/1 mL; MAGNESIUM PHOSPHATE, DIBASIC TRIHYDRATE 8 [hp_X]/1 mL; CLAVICEPS PURPUREA SCLEROTIUM 6 [hp_X]/1 mL
INACTIVE INGREDIENTS: ALCOHOL

Muscle Cramp Complex

Purpose:

Suggested use for one or more of the following symptoms:

Writers and music players cramps; cramps in hands, legs, calves, and feet. Muscle spasms in general.

Usage and Dosage:

For oral use only.

DOSAGE AND ADMINISTRATION

Adults:
In Acute Phase:
12-15 drops, every half hour until relief occurs
When Relief Occurs:
12-15 drops, 4-6 times per day
Children 2-12 years:
8-10 drops, 4-6 times per day

Warnings:

Keep out of reach of children.

WARNINGS

If symptoms persist, consult a physician.
Do not use if ring on bottom of cap is broken or missing.

Active Ingredients:

Anacardium orientale 6X, Belladonna 6X, Cactus grandiflorus 6X, Calcarea carbonica 12X, Carboneum sulphuratum 10X, Cuprum aceticum 4X, Magnesia phosphorica 8X, Secale cornutum 6X

Inactive Ingredients:

Alcohol, 20% USP

QUESTIONS

Manufactured by Nova Homeopathic Therapeutics Inc., Albuquerque, New Mexico USA 87109
1-800-225-8094

PACKAGE LABEL

Muscle Cramp Complex Product

Muscle Cramp Complex Bottle Label

Muscle Cramp Complex Box